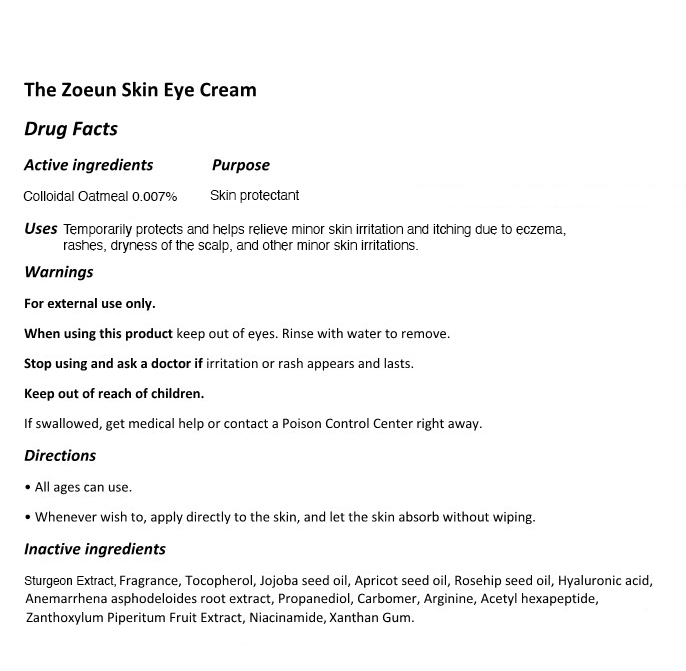 DRUG LABEL: The Zoeun Skin Eye Cream
NDC: 83636-116 | Form: CREAM
Manufacturer: Sturgeonbio Co.,Ltd.
Category: otc | Type: HUMAN OTC DRUG LABEL
Date: 20251001

ACTIVE INGREDIENTS: OATMEAL 0.007 g/100 mL
INACTIVE INGREDIENTS: FRAGRANCE 13576; STURGEON, UNSPECIFIED; ZANTHOXYLUM PIPERITUM FRUIT PULP; NIACINAMIDE; HYALURONIC ACID; ACETYL HEXAPEPTIDE-1; JOJOBA OIL; PROPANEDIOL; ARGININE; ROSA MOSCHATA OIL; CARBOMER HOMOPOLYMER, UNSPECIFIED TYPE; APRICOT SEED OIL; XANTHAN GUM; TOCOPHEROL; ANEMARRHENA ASPHODELOIDES ROOT

116 THE ZOEUN SKIN EYE CREAM

Active Ingredients

Colloidal Oatmeal 0.007%

Purpose

Skin Protectant.

Uses

Temporarily protects and helps relieve minor skin irritation and itching due to eczema, rashes, insect bites, and other minor skin irritations.

Warnings

- Keep out of reach of children.
- If swallowed, get medical help or contact a Poison Control Center right away.

Warnings

Stop using and ask a doctor if irritation or rash appears and lasts.

Warnings

When using this product keep out of eyes. Rinse with water to remove.

Warnings

For external use only.

Directions

- All ages can use.
- Whenever wish to, apply directly to the skin, and let the skin absorb without wiping.

Inactive Ingredients

Sturgeon Extract, Tocopherol, Simmondsia Chinensis (Jojoba) Seed Oil, Apricot Kernel Oil, Rosa Canina Seed Oil,
Camellia Japonica Seed Oil, Sodium Hyaluronate, Lavandula Angustifolia (Lavender) Flower Extract,
Jasminum Officinale (Jasmine) Flower Extract, Anemarrhena Asphodeloides Root Extract, Acetyl Hexapeptide-8,
Propanediol, Carbomer, Arginine, Zanthoxylum Piperitum Fruit Extract, Niacinamide, Xanthan Gum.